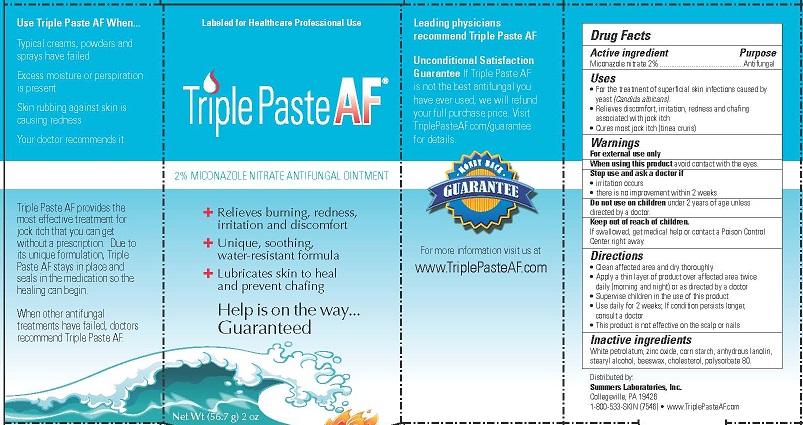 DRUG LABEL: TRIPLE
NDC: 11086-040 | Form: PASTE
Manufacturer: Summers Laboratories Inc
Category: otc | Type: HUMAN OTC DRUG LABEL
Date: 20231009

ACTIVE INGREDIENTS: MICONAZOLE NITRATE 2 g/100 g
INACTIVE INGREDIENTS: PETROLATUM; ZINC OXIDE; STARCH, CORN; LANOLIN; STEARYL ALCOHOL; YELLOW WAX; CHOLESTEROL; POLYSORBATE 80

SUMMERS LABS (as PLD) - TRIPLE PASTE AF (11086-040)

ACTIVE INGREDIENT

MICONAZOLE NITRATE 2%

PURPOSE

ANTIFUNGAL

Uses

- For the treatment of superficial skin infections caused by yeast (Candida albicans).
- Relieves discomfort, irritation, redness and chafing associated with jock itch
- Cures most jock itch (tinea cruris)

WARNINGS

FOR EXTERNAL USE ONLY

When using this product avoid contact with eyes

Stop use and ask a doctor if

- irritation occurs
- there is no improvement within 2 weeks

Do not use on children under 2 years of age unless directed by a doctor.

KEEP OUT OF REACH OF CHILDREN.

IF SWALLOWED, GET MEDICAL HELP OR CONTCT A POISON CONTROL CENTER RIGHT AWAY.

Directions

- Clean affected area and dry thoroughly
- Apply a thin layer of product over affected area twice daily (morning and night) or as directed by a doctor
- Supervise children in the use of this product
- Use daily for 2 weeks; If condition persists longer, consult a doctor
- This product is not effective on the scalp or nails

Inactive ingredients

White petrolatum, zinc oxide, corn starch, anhydrous lanolin, stearyl alcohol, beeswax, cholesterol, polysorbate 80.